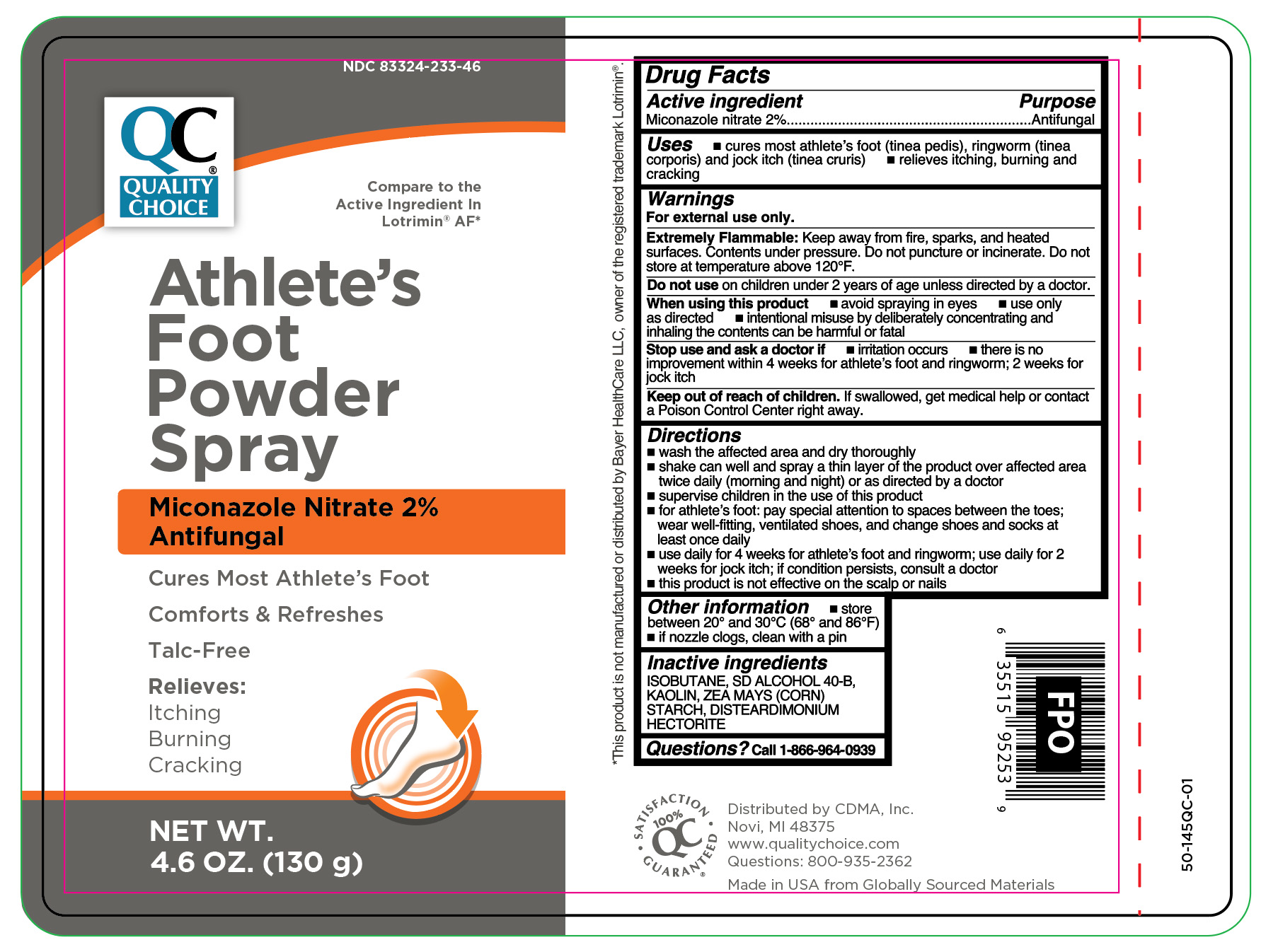 DRUG LABEL: Miconazole Nitrate
NDC: 83324-233 | Form: AEROSOL, POWDER
Manufacturer: Chain Drug Marketing Association
Category: otc | Type: HUMAN OTC DRUG LABEL
Date: 20251106

ACTIVE INGREDIENTS: MICONAZOLE NITRATE 20 mg/1 g
INACTIVE INGREDIENTS: ALCOHOL; ZEA MAYS (CORN) STARCH; ISOBUTANE; KAOLIN; DISTEARDIMONIUM HECTORITE

Quality Choice Antifungal Miconazole (Athlete's Foot) Powder Spray Talc-Free

Active ingredient

Miconazole nitrate 2%

Purpose

Antifungal

Uses

- cures most athlete's foot (tinea pedis), ringworm (tinea corporis) and jock itch (tinea cruris)
- relieves itching, burning and cracking

Warnings

For external use only.

Extremely Flammable:

Keep away from fire, sparks, and heated surfaces.Contents under pressure. Do not puncture or incinerate. Do not store at temperature above 120ºF.

Do not use

on children under 2 years of age unless directed by a doctor.

When using this product

- avoid spraying in eyes
- use only as directed
- intentional misuse by deliberately concentrating and inhaling the contents can be harmful or fatal.

Stop use and ask a doctor if

- irritation occurs
- there is no improvement within 4 weeks for athlete's foot and ringworm; 2 weeks for jock itch

Keep out of reach of children.

If swallowed, get medical help or contact a Poison Control Central right away.

Directions

- wash the affected area and dry thoroughly
- shake can well and spray a thin layer of the product over affected area twice daily (morning and night) or as directed by a doctor
- supervise children in the use of this product
- for athlete's foot: pay special attention to spaces between the toes; wear well-fitting, ventilated shoes, and change shoes and socks at least once daily
- use daily for 4 weeks for athlete's foot and ringworm; use daily for 2 weeks for jock itch, if conditions persist, consult a doctor
- this product is not effective on the scalp or nails

Other information

- store between 20º and 30ºC (68º and 86ºF)
- if nozzle clogs, clean with a pin

Inactive ingredients

ISOBUTANE, SD ALCOHOL 40-B, KAOLIN, ZEA MAYS (CORN) STARCH, DISTEARDIMONIUM HECTORITE

Questions?

Call 1-866-964-0939

Principal Display Panel

QC

Quality Choice

Athlete's

Foot

Powder

Spray

Miconazole Nitrate 2%

Antifungal

Cures Most Athlete's Foot

Comforts & Refreshes

Talc- Free

Relieves:

Itching

Burning

Cracking

NET WT.

4.6 OZ. (130 g)